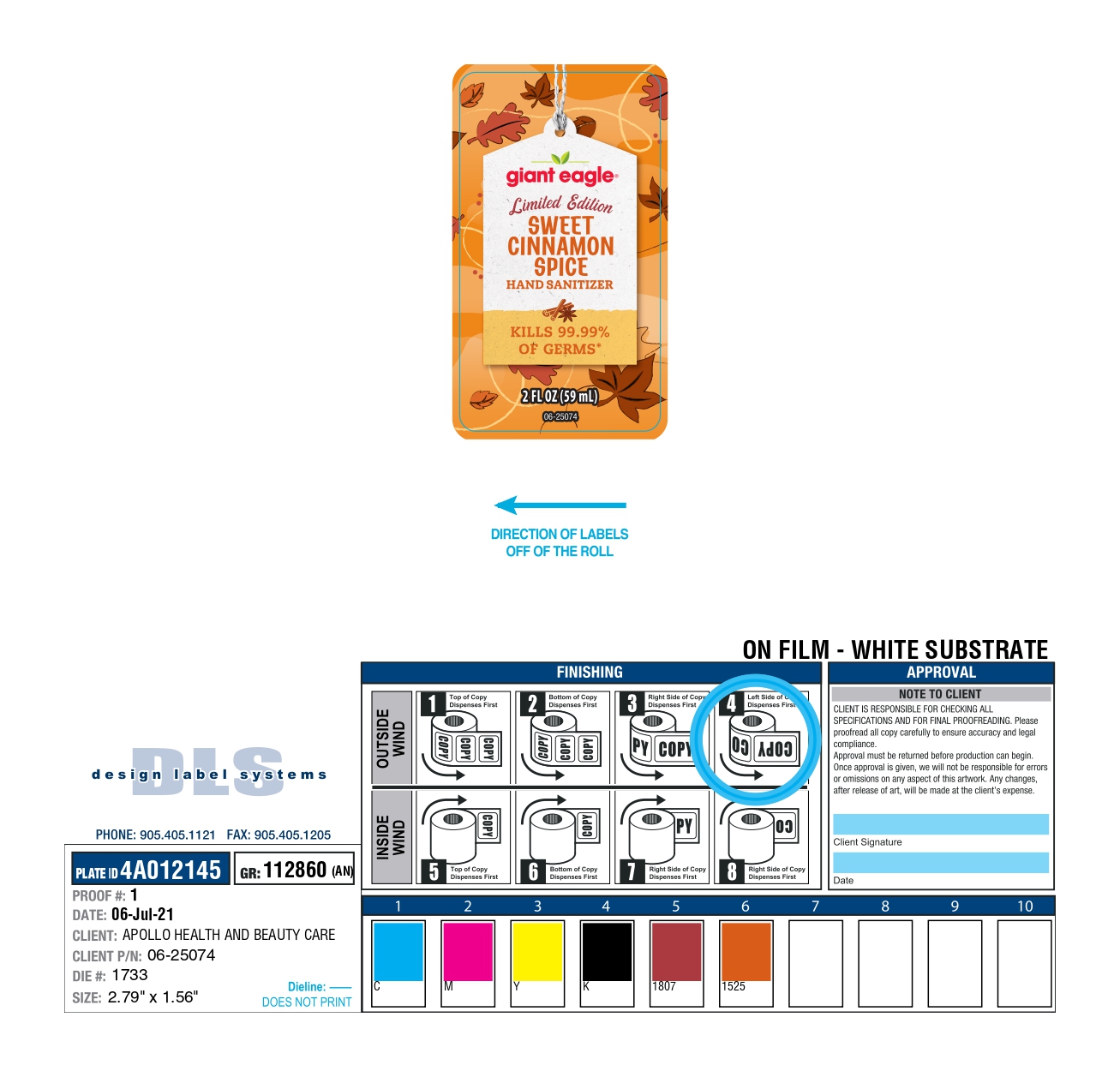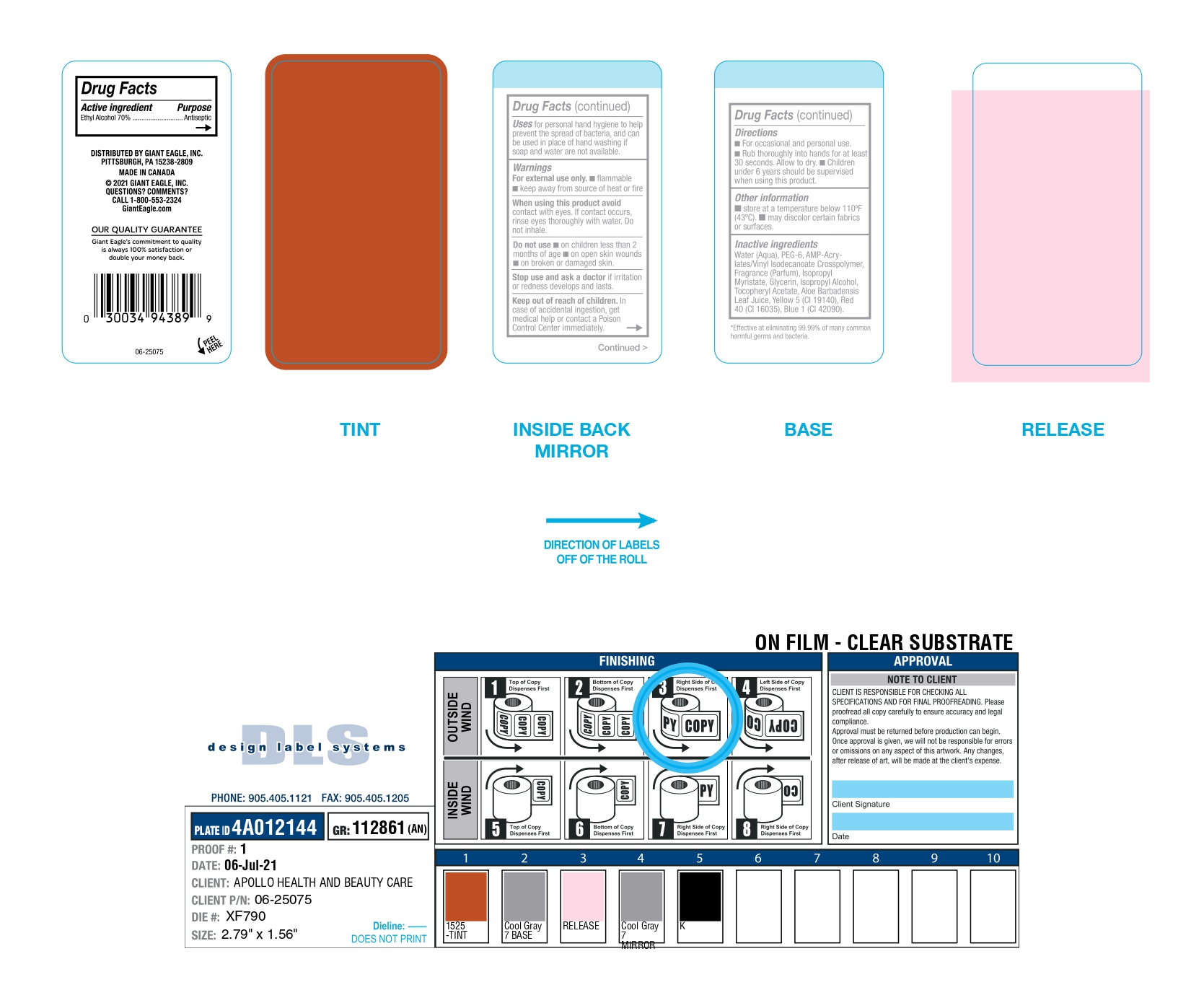 DRUG LABEL: Sweet Cinnamon Hand Sanitizer
NDC: 63148-726 | Form: GEL
Manufacturer: Apollo Health and Beauty Care
Category: otc | Type: HUMAN OTC DRUG LABEL
Date: 20250105

ACTIVE INGREDIENTS: ALCOHOL 700 mg/1 mL
INACTIVE INGREDIENTS: WATER; POLYETHYLENE GLYCOL 300; ACRYLATES/VINYL ISODECANOATE CROSSPOLYMER (10000 MPA.S NEUTRALIZED AT 0.5%); ISOPROPYL MYRISTATE; GLYCERIN; ISOPROPYL ALCOHOL; .ALPHA.-TOCOPHEROL ACETATE, DL-; ALOE VERA LEAF; BASIC YELLOW 5; FD&C RED NO. 40; DIRECT BLUE 1

NDC- 63148-726

Active Ingredients

Ethyl Alcohol (70%)

Purpose

Antiseptic

Uses

For Personal hand hygiene to help prevent the spread of bacteria and can be used in place of hand washing if soap and water are not available.

Warnings

- For External use only
- Flammable
- Keep away from source of heat or fire.

When using this product

Avoid contact with eyes. If contact occurs, rinse eyes thoroughly with water. Do not Inhale.

Do not use

- on children less than 2 months of age
- on open skin wounds
- on broken or damaged skin

Stop use and ask a doctor

If Irritation or redness develops and lasts.

Keep out of reach of children

In case of accidental ingestion, get medical help or contact a Poison Control Centre immediately

Directions

- For occasional and personal use
- Rub thoroughly into hands for at least 30 seconds. Allow to dry
- Children under 6 years should be supervised when using this product

Other Information

- Store at a temperature below 110^0F (43^0C)
- May discolor certain fabrics or surfaces

Inactive Ingredients

Water (Aqua), PEG-6, AMP-Acrylates/Vinyl Isodecanate Crosspolymer, Fragrance (Parfum), Isopropyl Myristate, Glycerin, Isopropyl Alcohol, Tocopheryl Acetate, Aloe Barbadensis Leaf Juice, Yellow 5 (Cl19140), Red 40 (Cl16035) Blue 1 (Cl42090)